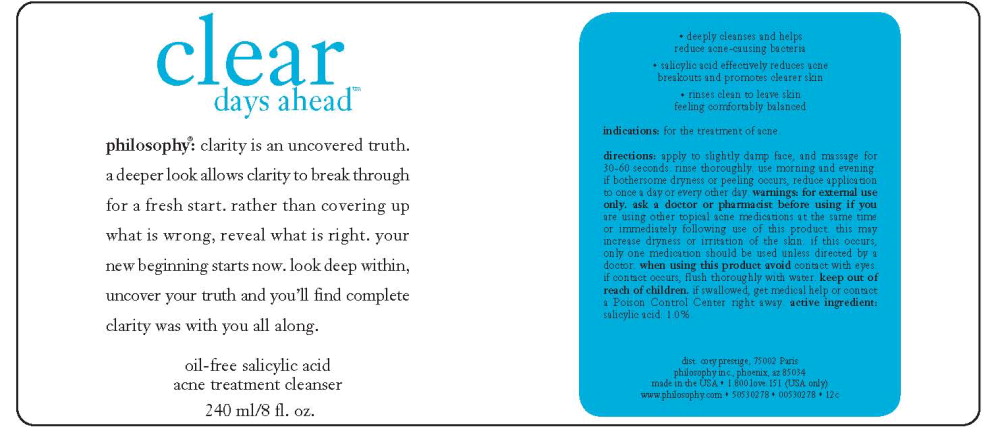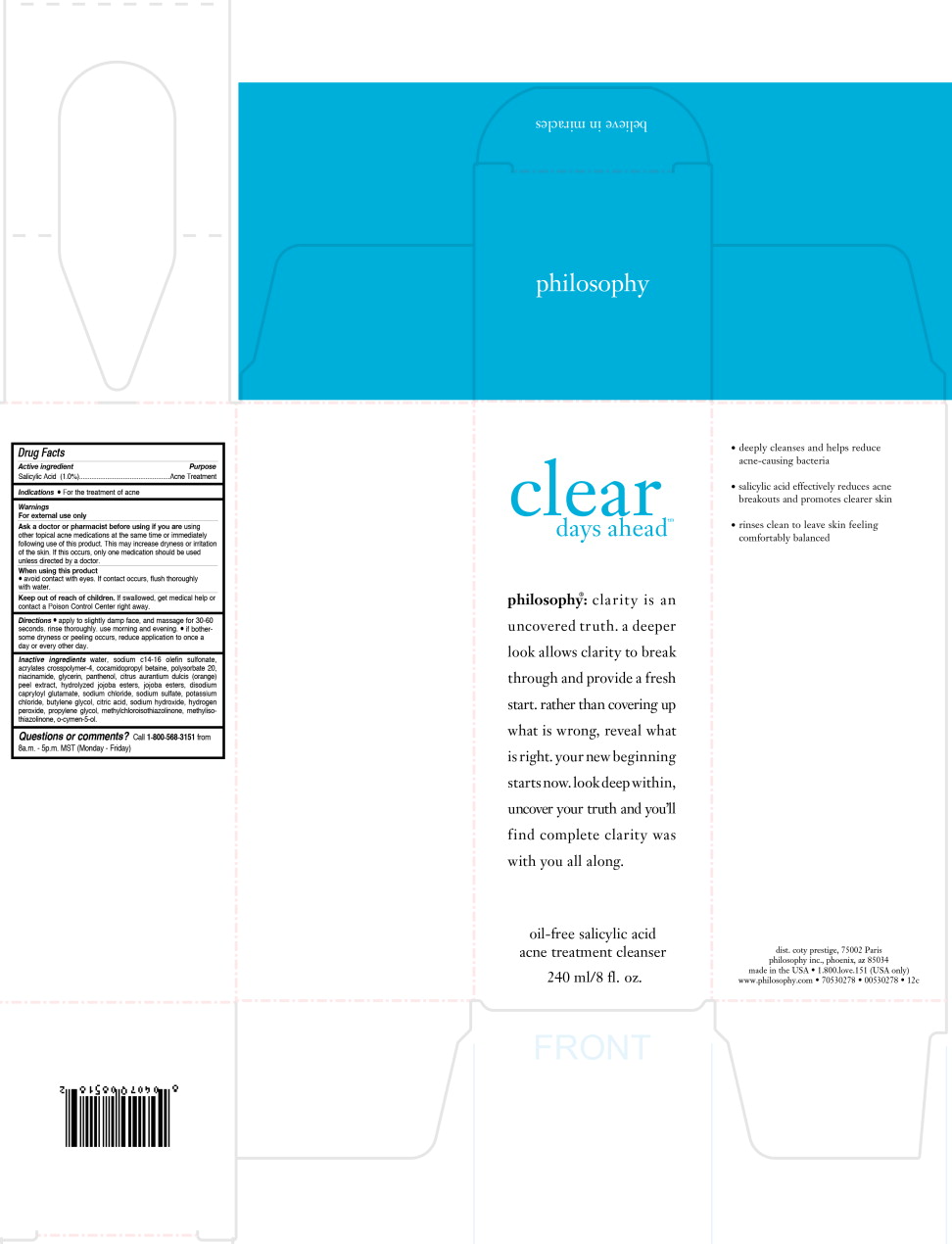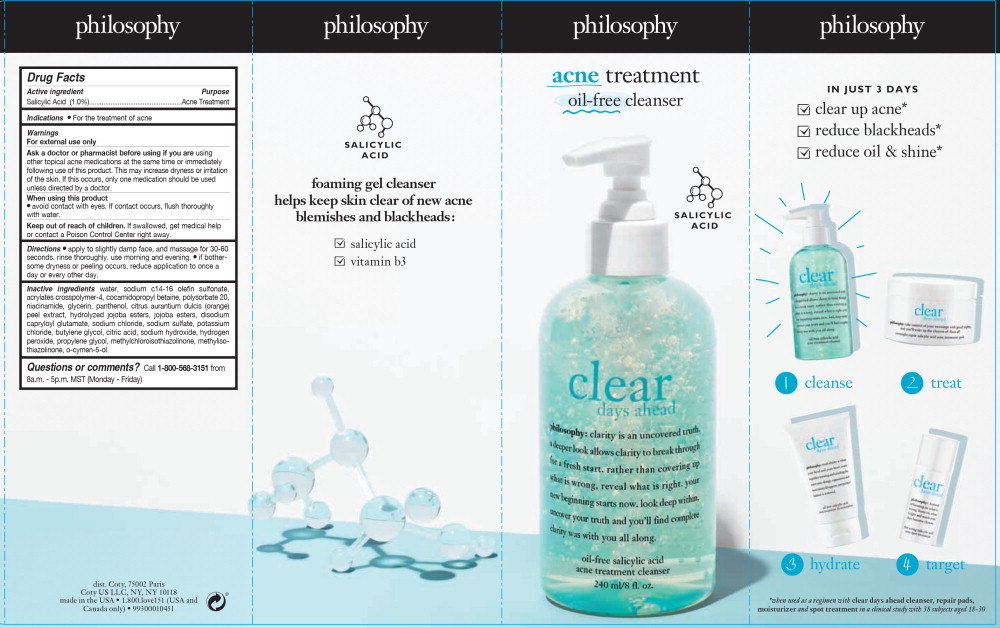 DRUG LABEL: clear days ahead
NDC: 50184-1005 | Form: LIQUID
Manufacturer: Philosophy Inc.
Category: otc | Type: HUMAN OTC DRUG LABEL
Date: 20251217

ACTIVE INGREDIENTS: SALICYLIC ACID 2.4 g/240 mL
INACTIVE INGREDIENTS: WATER; SODIUM C14-16 OLEFIN SULFONATE; COCAMIDOPROPYL BETAINE; POLYSORBATE 20; NIACINAMIDE; GLYCERIN; PANTHENOL; ORANGE PEEL; HYDROLYZED JOJOBA ESTERS (ACID FORM); SODIUM CHLORIDE; SODIUM SULFATE; POTASSIUM CHLORIDE; BUTYLENE GLYCOL; CITRIC ACID MONOHYDRATE; SODIUM HYDROXIDE; HYDROGEN PEROXIDE; PROPYLENE GLYCOL; METHYLCHLOROISOTHIAZOLINONE; O-CYMEN-5-OL

Drug Facts

Active ingredient

Salicylic Acid (1.0%)

Purpose

Acne Treatment

Indications

- For the treatment of acne

Warnings

For external use only

Ask a doctor or pharmacist before using if you are using other topical acne medications at the same time or immediately following use of this product. This may increase dryness or irritation of the skin. If this occurs, only one medication should be used

unless directed by a doctor.

When using this product

- avoid contact with eyes. If contact occurs, flush thoroughly with water.

Keep out of reach of children.

If swallowed, get medical help or contact a Poison Control Center right away.

Directions

- apply to slightly damp face, and massage for 30-60 seconds. rinse thoroughly. use morning and evening.
- if bothersome dryness or peeling occurs, reduce application to once a day or every other day.

Inactive ingredients

water, sodium c14-16 olefin sulfonate, acrylates crosspolymer-4, cocamidopropyl betaine, polysorbate 20, niacinamide, glycerin, panthenol, citrus aurantium dulcis (orange) peel extract, hydrolyzed jojoba esters, jojoba esters, disodium capryloyl glutamate, sodium chloride, sodium sulfate, potassium chloride, butylene glycol, citric acid, sodium hydroxide, hydrogen peroxide, propylene glycol, methylchloroisothiazolinone, methylisothiazolinone, o-cymen-5-ol.

Questions or comments?

Call 1-800-568-3151 from 8a.m. - 5p.m. MST (Monday - Friday)

Principal Display Panel - 240 ml Sleeve Label

philosophy

acne treatment

oil-free cleanser

salicylic acid

Principal Display Panel - 240 ml Box Label

clear

days ahead™

philosophy®: clarity is an
uncovered truth. a deeper
look allows clarity to break
through and provide a fresh
start. rather than covering up
what is wrong, reveal what
is right. your new beginning
starts now. look deep within,
uncover your truth and you'll
find complete clarity was
with you all along.

oil-free salicylic acid

acne treatment cleanser

240 ml/8 fl. oz.

Principal Display Panel - 240 ml Bottle Label

clear

days ahead™

philosophy®: clarity is an uncovered truth.
a deeper look allows clarity to break through
and provide a fresh start. rather than covering up
what is wrong, reveal what is right. your
new beginning starts now. look deep within,
uncover your truth and you'll find complete
clarity was with you all along.

oil-free salicylic acid

acne treatment cleanser

240 ml/8 fl. oz.